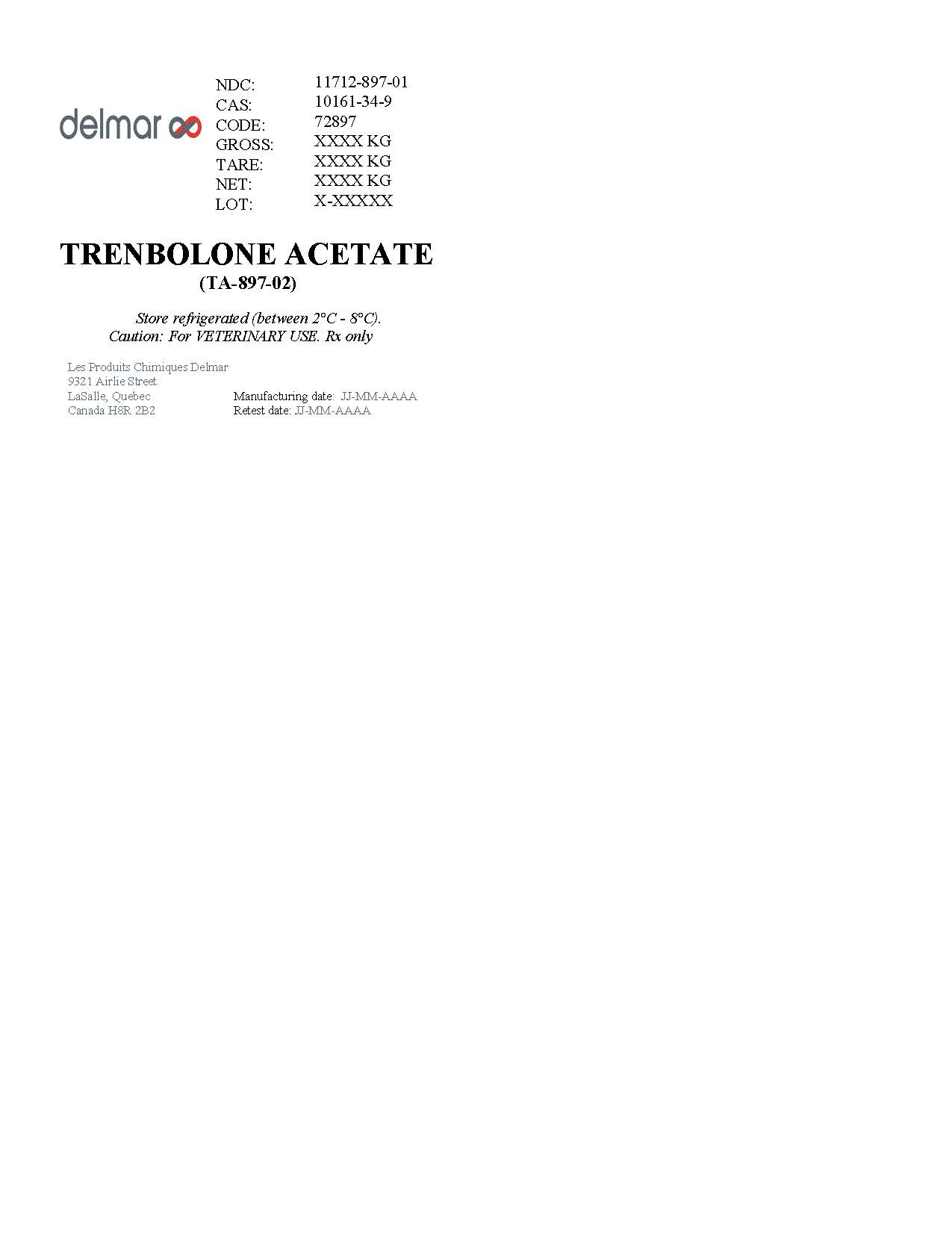 DRUG LABEL: Trenbolone Acetate
NDC: 11712-897 | Form: POWDER
Manufacturer: Delmar Chemical Inc
Category: other | Type: BULK INGREDIENT - ANIMAL DRUG
Date: 20231213

ACTIVE INGREDIENTS: TRENBOLONE ACETATE 1 kg/1 kg

Trenbolone Acetate (TA-897-02)